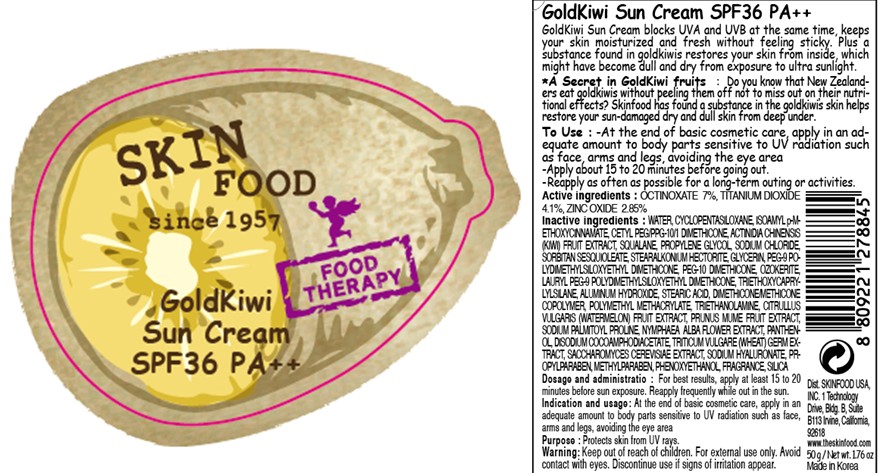 DRUG LABEL: GOLDKIWI SUN
NDC: 76214-034 | Form: CREAM
Manufacturer: SKINFOOD CO., LTD.
Category: otc | Type: HUMAN OTC DRUG LABEL
Date: 20111006

ACTIVE INGREDIENTS: OCTINOXATE 3.5 g/50 g; TITANIUM DIOXIDE 2.05 g/50 g; ZINC OXIDE 1.42 g/50 g
INACTIVE INGREDIENTS: WATER; CYCLOMETHICONE 5; KIWI FRUIT; SILICON DIOXIDE; SQUALANE; PROPYLENE GLYCOL; SODIUM CHLORIDE; SORBITAN SESQUIOLEATE; GLYCERIN; TRIETHOXYCAPRYLYLSILANE; ALUMINUM HYDROXIDE; STEARIC ACID; METHYLPARABEN; PHENOXYETHANOL; PROPYLPARABEN; TROLAMINE; WATERMELON; PRUNUS MUME FRUIT; SODIUM PALMITOYL PROLINE; NYMPHAEA ALBA FLOWER; PANTHENOL; DISODIUM COCOAMPHODIACETATE; WHEAT GERM; SACCHAROMYCES CEREVISIAE; HYALURONATE SODIUM

Drug Facts

ACTIVE INGREDIENT

Active ingredients: OCTINOXATE 7%, TITANIUM DIOXIDE 4.1%, ZINC OXIDE 2.85%

Inactive ingredients:
WATER, CYCLOPENTASILOXANE, ISOAMYL p-METHOXYCINNAMATE, CETYL PEG/PPG-10/1 DIMETHICONE, ACTINIDIA CHINENSIS (KIWI) FRUIT EXTRACT, SQUALANE, PROPYLENE GLYCOL, SODIUM CHLORIDE, SORBITAN SESQUIOLEATE, STEARALKONIUM HECTORITE, GLYCERIN, PEG-9 POLYDIMETHYLSILOXYETHYL DIMETHICONE, PEG-10 DIMETHICONE, OZOKERITE, LAURYL PEG-9 POLYDIMETHYLSILOXYETHYL DIMETHICONE, TRIETHOXYCAPRYLYLSILANE, ALUMINUM HYDROXIDE, STEARIC ACID, DIMETHICONE/METHICONE COPOLYMER, POLYMETHYL METHACRYLATE, TRIETHANOLAMINE, CITRULLUS VULGARIS (WATERMELON) FRUIT EXTRACT, PRUNUS MUME FRUIT EXTRACT, SODIUM PALMITOYL PROLINE, NYMPHAEA ALBA FLOWER EXTRACT, PANTHENOL, DISODIUM COCOAMPHODIACETATE, TRITICUM VULGARE (WHEAT) GERM EXTRACT, SACCHAROMYCES CEREVISIAE EXTRACT, SODIUM HYALURONATE, PROPYLPARABEN, METHYLPARABEN, PHENOXYETHANOL, FRAGRANCE, SILICA

Purpose: Protects skin from UV rays.

Warnings:
For external use only.
Avoid contact with eyes.
Discontinue use if signs of irritation appear.

Keep out of reach of children:
Keep out of reach of children.

Indication and usage:
At the end of basic cosmetic care, apply in an adequate amount to body parts sensitive to UV radiation such as face, arms and legs, avoiding the eye area.

Dosage and administration:
For best results, apply at least 15 to 20 minutes before sun exposure.
Reapply frequently while out in the sun.